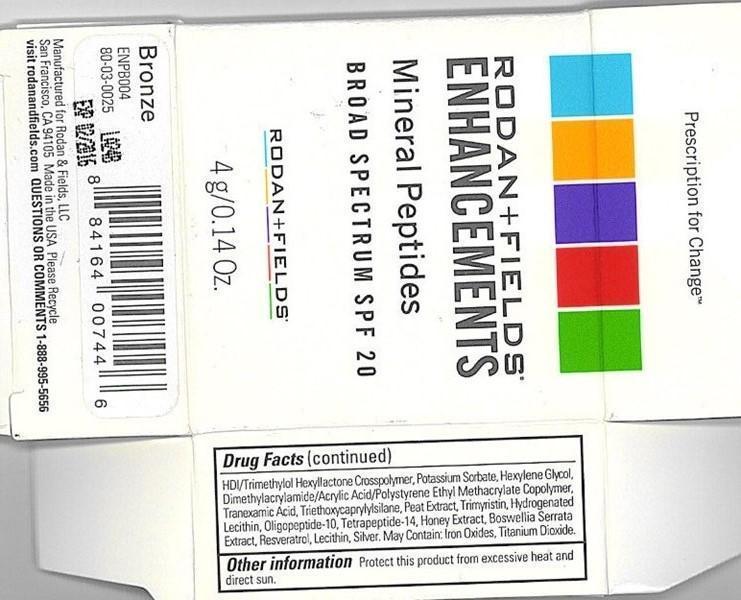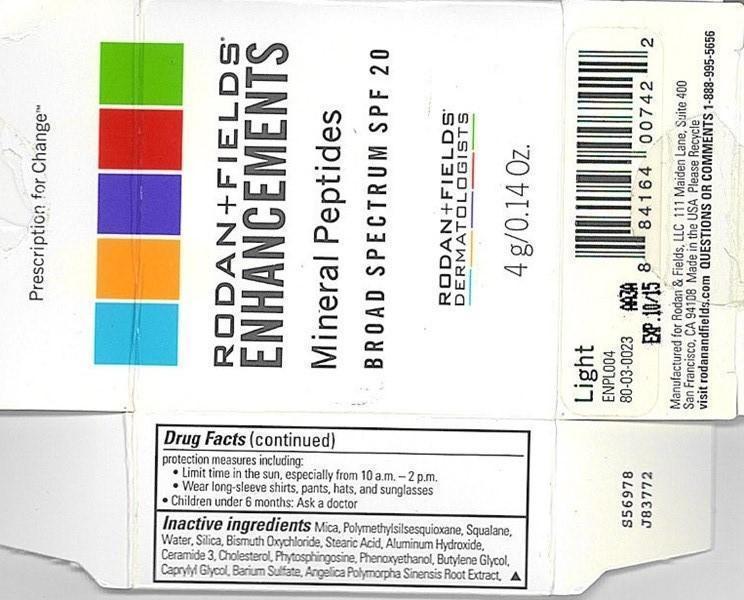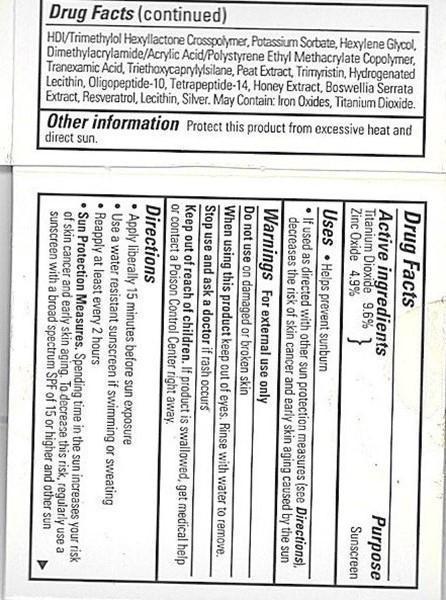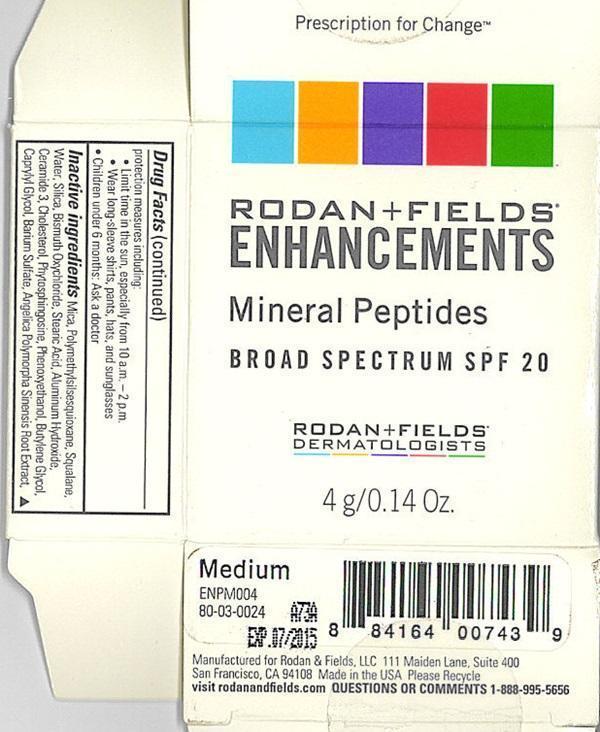 DRUG LABEL: RODAN and FIELDS ENHANCEMENTS
NDC: 54111-119 | Form: POWDER
Manufacturer: Bentley Laboratories, LLC
Category: otc | Type: HUMAN OTC DRUG LABEL
Date: 20231219

ACTIVE INGREDIENTS: TITANIUM DIOXIDE 0.38400 g/4 g; ZINC OXIDE 0.19600 g/4 g
INACTIVE INGREDIENTS: MICA; POLYMETHYLSILSESQUIOXANE (4.5 MICRONS); SQUALANE; WATER; SILICON DIOXIDE; BISMUTH OXYCHLORIDE; STEARIC ACID; ALUMINUM HYDROXIDE; CERAMIDE 3; CHOLESTEROL; PHYTOSPHINGOSINE; PHENOXYETHANOL; BUTYLENE GLYCOL; CAPRYLYL GLYCOL; BARIUM SULFATE; ANGELICA SINENSIS ROOT; HEXAMETHYLENE DIISOCYANATE/TRIMETHYLOL HEXYLLACTONE CROSSPOLYMER ; POTASSIUM SORBATE; HEXYLENE GLYCOL; TRANEXAMIC ACID; TRIETHOXYCAPRYLYLSILANE; TRIMYRISTIN; HYDROGENATED SOYBEAN LECITHIN; HONEY; INDIAN FRANKINCENSE; RESVERATROL; LECITHIN, SOYBEAN; SILVER; FERRIC OXIDE RED; FERRIC OXIDE YELLOW

Drug Facts Active ingredients

Titanium Dioxide 9.6%
Zinc Oxide 4.9%

Purpose

Sunscreen

Keep out of each of children.

Keep out of reach of children.

If product is swallowed, get medical help or contact a Poison Control Center right away.

Uses

- Helps prevent sunburn

Warnings

For external use only

Do not use

on damaged or broken skin

When using this product

keep out of eyes. Rinse with water to remove.

Stop use and ask a doctor

if rash occurs

Directions

- Apply liberally 15 minutes before sun exposure
- Use a water resistant sunscreen if swimming or sweating
- Reapply at least every 2 hours
- Sun Protection Measures. Spending time in the sun increases your risk of skin cancer and early skin aging. To decrease this risk, regularly use a sunscreen with a broad spectrum of 15 or higher and other sun protection measures including:
-
  - Limit time in the sun, especially from 10 a.m. - 2 p.m.
  - Wear long sleeve shirts, pants, hats, and sunglasses
  - Children under 6 months: Ask a doctor

Inactive ingredients

Mica, Polymetylsilsesquioxane, Squalane, Water, Silia, Bismuth Oxychloride, Stearic Acid, Aluminum Hydroxide, Ceramide 3, Cholesterol, Phytosphingosine, Phenoxyethanol, Butylene Glycol, Caprylyl Glycol, Barium Sulfate, Angelica Polymorpha Sinensis Root Extract, HDI/Trimethylol Hexyllactone Crosspolymer, Potassium Sorbate, Hexylene Glycol, Dimethylacrlamide/Acrylic Acid/Polystyrene Ethyl Methacrylate Copolymer, Tranexamic Acid, Triethoxycaprylylsilane, Peat Extract, Trimyristin, Hydrogenated Lecithin, Oligopeptide-10, Tetrapeptide-14, Honey Extrac, Boswellia Serrata Extract, Resveratrol Lecithin, Silver. May contain: Iron Oxides, Titanium Dioxide.

Other information

Protect this product from excessive heat and direct sun.

Rodan + Fields ENHANCEMENTS - Light, Medium, Bronze Product Labels

escription for Change™

RODAN+FIELDS®
ENHANCEMENTS

Mineral Peptides

BROAD SPECTRUM SPF 20

RODAN+FIELDS®
DERMATOLOGISTS

4g/0.14 Oz.

Manufactured for Rodan and Fields, LLC 111 Maiden Lane, Suite 400 San Francisco CA 94108 Made in the USA Please Recycle

visit rodanand fields.com QUESTIONS OR COMMENTS 1-888-995-5656

Light
ENPL004
08-03-0023

Medium
ENPM004
80-03-0024

Bronze
ENPB004
80-03-0025

res